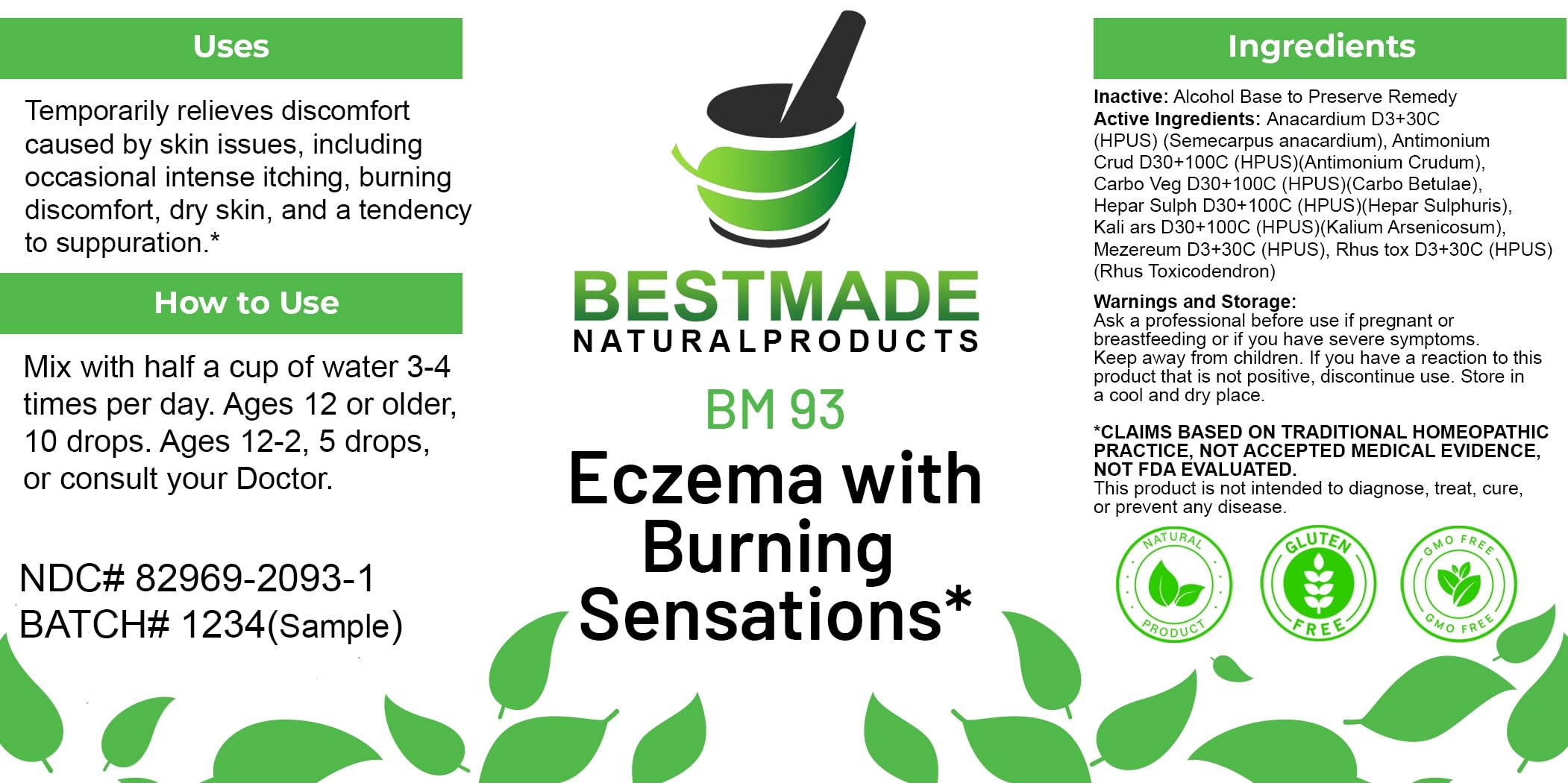 DRUG LABEL: Bestmade Natural Products BM93
NDC: 82969-2093 | Form: LIQUID
Manufacturer: Bestmade Natural Products
Category: homeopathic | Type: HUMAN OTC DRUG LABEL
Date: 20250203

ACTIVE INGREDIENTS: TOXICODENDRON PUBESCENS LEAF 30 [hp_C]/30 [hp_C]; SEMECARPUS ANACARDIUM JUICE 30 [hp_C]/30 [hp_C]; POTASSIUM ARSENITE ANHYDROUS 30 [hp_C]/30 [hp_C]; ANTIMONY TRISULFIDE 30 [hp_C]/30 [hp_C]; CALCIUM SULFIDE 30 [hp_C]/30 [hp_C]; DAPHNE MEZEREUM BARK 30 [hp_C]/30 [hp_C]; ACTIVATED CHARCOAL 30 [hp_C]/30 [hp_C]
INACTIVE INGREDIENTS: ALCOHOL 30 [hp_C]/30 [hp_C]

BM93

DOSAGE AND ADMINISTRATION

How to Use

Mix with half a cup of water 3-4 times per day. Ages 12 or older, 10 drops. Ages 12-2, 5 drops, or consult your Doctor.

INACTIVE INGREDIENT

Ingredients

Inactive: Alcohol Base to Preserve Remedy

ACTIVE INGREDIENT

Active Ingredients: Anacardium D3+30C (HPUS) (Semecarpus anacardium), Antimonium Crud D30+100C (HPUS)(Antimonium Crudum), Carbo Veg D30+100C (HPUS)(Carbo Betulae), Hepar Sulph D30+100C (HPUS)(Hepar Sulphuris), Kali ars D30+100C (HPUS)(Kalium Arsenicosum), Mezereum D3+30C (HPUS), Rhus tox D3+30C (HPUS)(Rhus Toxicodendron)

Uses

Temporarily relieves discomfort caused by skin issues, including occasional intense itching, burning discomfort, dry skin, and a tendency to suppuration.*

*CLAIMS BASED ON TRADITIONAL HOMEOPATHIC PRACTICE, NOT ACCEPTED MEDICAL EVIDENCE, NOT FDA EVALUATED.

This product is not intended to diagnose, treat, cure, or prevent any disease.

Uses

Temporarily relieves discomfort caused by skin issues, including occasional intense itching, burning discomfort, dry skin, and a tendency to suppuration.*

*CLAIMS BASED ON TRADITIONAL HOMEOPATHIC PRACTICE, NOT ACCEPTED MEDICAL EVIDENCE, NOT FDA EVALUATED.

This product is not intended to diagnose, treat, cure, or prevent any disease.

KEEP OUT OF REACH OF CHILDREN

Warnings and Storage:

Ask a professional before use if pregnant or breastfeeding or if you have severe symptoms. Keep away from children. If you have a reaction to this product that is not positive, discontinue use. Store in a cool and dry place.

Warnings and Storage:

Ask a professional before use if pregnant or breastfeeding or if you have severe symptoms. Keep away from children. If you have a reaction to this product that is not positive, discontinue use. Store in a cool and dry place.

*CLAIMS BASED ON TRADITIONAL HOMEOPATHIC PRACTICE, NOT ACCEPTED MEDICAL EVIDENCE, NOT FDA EVALUATED.

This product is not intended to diagnose, treat, cure, or prevent any disease.

Entire package label